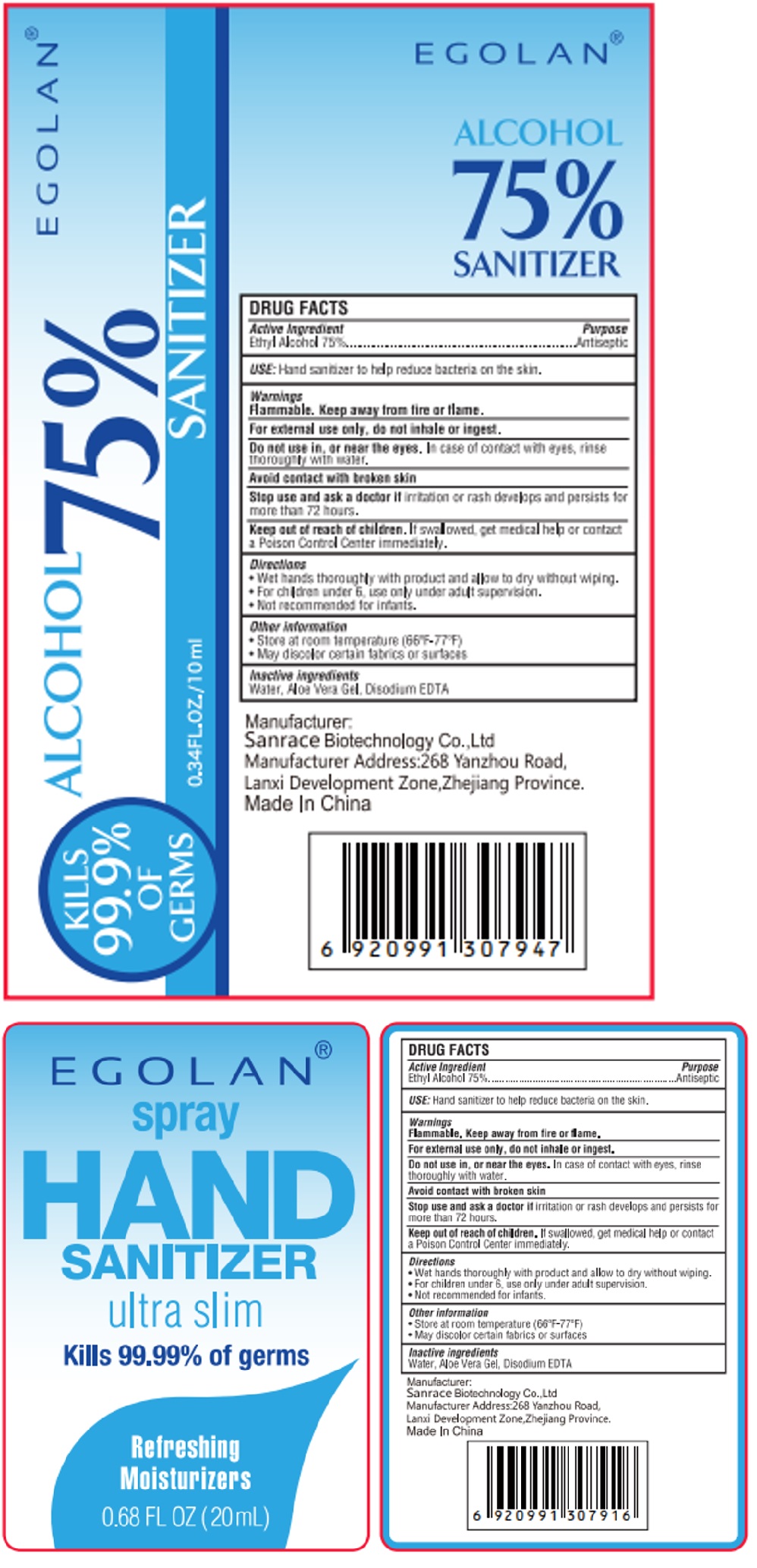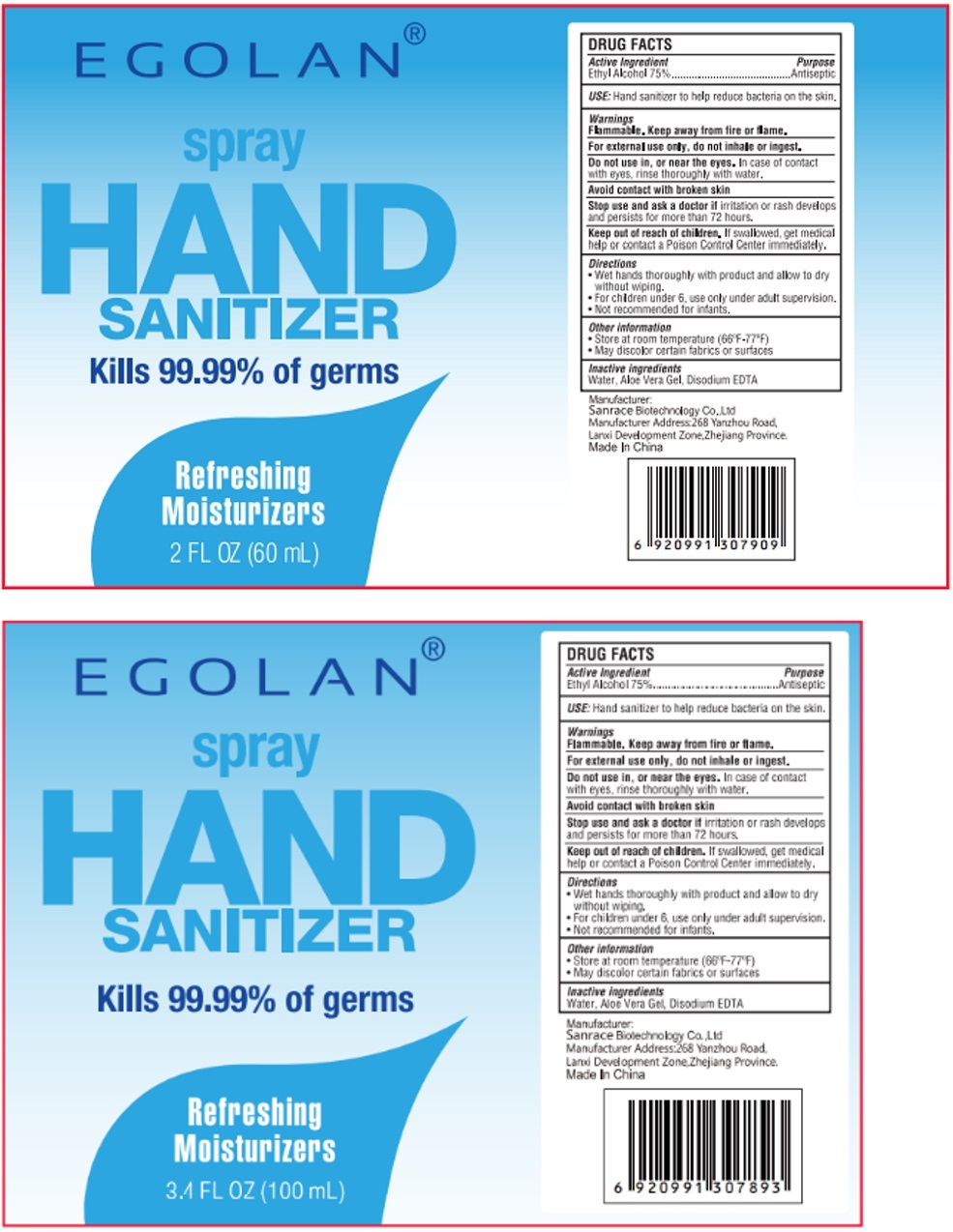 DRUG LABEL: EGOLAN
NDC: 75448-024 | Form: SPRAY
Manufacturer: Sanrace Biotechnology Co., Ltd.
Category: otc | Type: HUMAN OTC DRUG LABEL
Date: 20200615

ACTIVE INGREDIENTS: ALCOHOL 75 mL/100 mL
INACTIVE INGREDIENTS: WATER; ALOE VERA LEAF; EDETATE DISODIUM ANHYDROUS

EGOLAN® Spray HAND SANITIZER

Active Ingredient

Ethyl Alcohol 75%

Purpose

Antiseptic

INDICATIONS AND USAGE

USE: Hand Sanitizer to help reduce bacteria on the skin.

Warnings

Flammable. Keep away from fire or flame.

For external use only. do not inhale or ingest.

Do not use in, or near the eyes. In case of contact with eyes, rinse thoroughly with water.

Avoid contact with broken skin.

Stop use and ask a doctor if irritation or rash develops and persists for more than 72 hours.

Keep out of reach of children. If swallowed, get medical help or contact a Poison Control Center immediately.

Directions

• Wet hands thoroughly with product and allow to dry without wiping.

• For children under 6, use only under adult supervision.

• Not recommended for infants

Other Information

• Store at room temperature (66°F-77°F)

• May discolor certain fabrics or surfaces

Inactive ingredients

Water, Aloe Vera Gel, Disodium EDTA

Kills 99.99% of germs

Refreshing Moisturizers

Manufacturer:

Sanrace Biotechnology Co., Ltd

Manufacturer Address: 268, Yanzhou Road,

Lanxi Development Zone, Zhejiang Province.

Made In China.